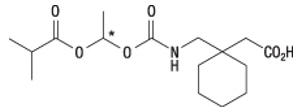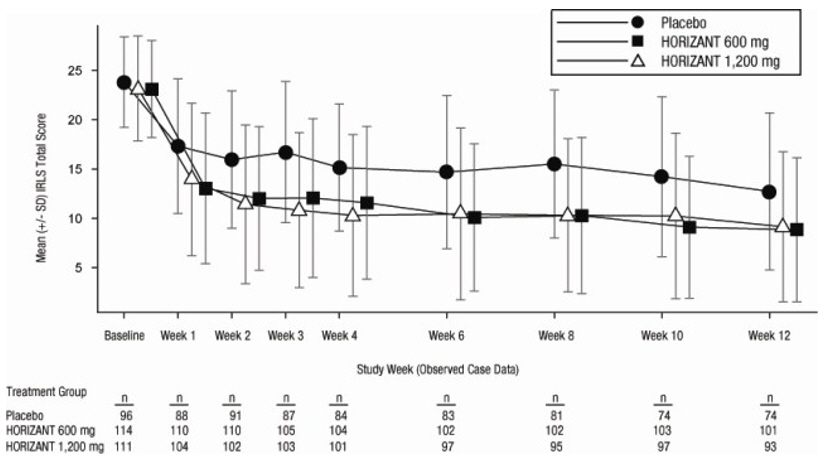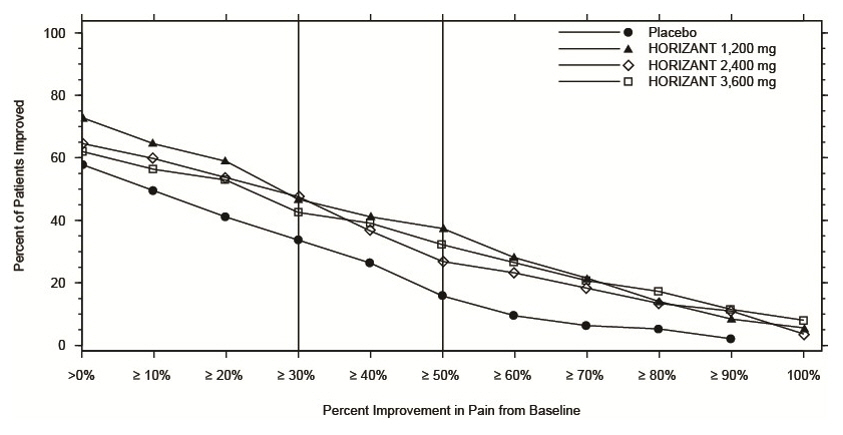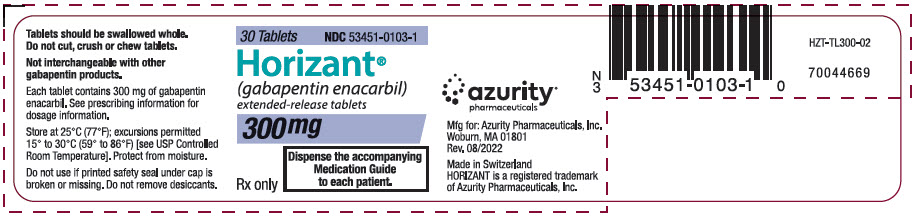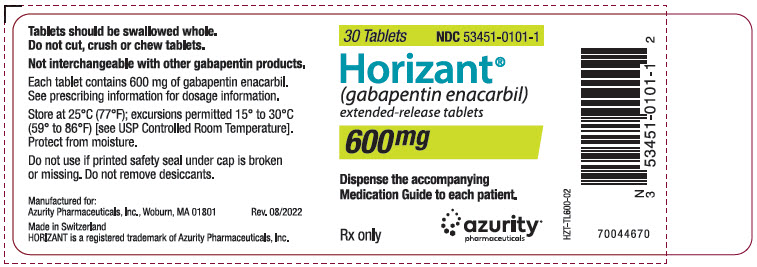 DRUG LABEL: Horizant
NDC: 53451-0103 | Form: TABLET, EXTENDED RELEASE
Manufacturer: Azurity Pharmaceuticals, Inc. (formerly Arbor Pharmaceuticals)
Category: prescription | Type: HUMAN PRESCRIPTION DRUG LABEL
Date: 20250428

ACTIVE INGREDIENTS: GABAPENTIN ENACARBIL 300 mg/1 1
INACTIVE INGREDIENTS: SILICON DIOXIDE; DIBASIC CALCIUM PHOSPHATE DIHYDRATE; GLYCERYL DIBEHENATE; MAGNESIUM STEARATE; SODIUM LAURYL SULFATE; TALC

HIGHLIGHTS OF PRESCRIBING INFORMATION

These highlights do not include all the information needed to use HORIZANT safely and effectively. See full prescribing information for HORIZANT.
HORIZANT®(gabapentin enacarbil) extended-release tablets, for oral use
Initial U.S. Approval: 2011

RECENT MAJOR CHANGES

Warnings and Precautions (5.4, 5.5) 04/2025

1 INDICATIONS AND USAGE

HORIZANT is indicated for:

- treatment of moderate-to-severe primary Restless Legs Syndrome (RLS) in adults. (1.1)
- management of postherpetic neuralgia (PHN) in adults. (1.2)

2 DOSAGE AND ADMINISTRATION

Instruct patients to swallow tablets whole and not to cut, crush, or chew tablets. Take with food. (2.1)

RLS: 600 mg once daily taken at about 5 PM. (2.2)

- A dose of 1,200 mg once daily provided no additional benefit compared with the 600-mg dose, but caused an increase in adverse reactions. (2.2)
- If the dose is not taken at the recommended time, the next dose should be taken the following day as prescribed. (2.2)

PHN: The starting dose is 600 mg in the morning for 3 days, then increase to 600 mg twice daily beginning on day 4. (2.3)

- A daily dose greater than 1,200 mg provided no additional benefit. (2.3)
- If the dose is not taken at the recommended time, skip this dose, and the next dose should be taken at the time of next scheduled dose. (2.3)

Patients with renal impairment: Doses of HORIZANT must be adjusted in accordance with renal function. (2.4)

3 DOSAGE FORMS AND STRENGTHS

Extended-Release Tablets: 300 mg and 600 mg. (3)

4 CONTRAINDICATIONS

None. (4)

5 WARNINGS AND PRECAUTIONS

- Driving impairment: Warn patients not to drive until they have gained sufficient experience with HORIZANT to assess whether it will impair their ability to drive. (5.1)
- Somnolence/sedation and dizziness: May impair the patient's ability to operate complex machinery. (5.2)
- HORIZANT is not substitutable with other gabapentin products. (5.3)
- Suicidal thoughts or behaviors: HORIZANT is a prodrug of gabapentin, an antiepileptic drug (AED). AEDs increase the risk of suicidal thoughts or behaviors. Monitor for suicidal thoughts or behaviors. (5.4)
- Abrupt or rapid discontinuation may increase the risk for seizures. Withdrawal symptoms, or suicidal behavior and ideation have been observed after discontinuation. (5.5)
- Respiratory depression: May occur with HORIZANT when used with concomitant central nervous system (CNS) depressants or in the setting of concurrent respiratory impairment. Monitor patients and adjust dosage as appropriate (5.6).

6 ADVERSE REACTIONS

- RLS: Most common adverse reactions (≥10% and at least 2 times the rate of placebo) were somnolence/sedation and dizziness. (6.1)
- PHN: Most common adverse reactions (≥10% and greater than placebo) were dizziness, somnolence, and headache. (6.1)

To report SUSPECTED ADVERSE REACTIONS, contact Azurity Pharmaceuticals, Inc. at 1-800-461-7449 or FDA at 1-800-FDA-1088 or www.fda.gov/medwatch.

8 USE IN SPECIFIC POPULATIONS

Pregnancy: Based on animal data, may cause fetal harm. (8.1)

FULL PRESCRIBING INFORMATION

1 INDICATIONS AND USAGE

1.1 Treatment of Restless Legs Syndrome

HORIZANT®is indicated for the treatment of moderate-to-severe primary Restless Legs Syndrome (RLS) in adults.

HORIZANT is not recommended for patients who are required to sleep during the daytime and remain awake at night.

1.2 Management of Postherpetic Neuralgia

HORIZANT is indicated for the management of postherpetic neuralgia (PHN) in adults.

2 DOSAGE AND ADMINISTRATION

2.1 Dosage and Administration Overview

Tablets should be swallowed whole and should not be cut, crushed, or chewed.

Tablets should be taken with food.

HORIZANT is not substitutable with other gabapentin products because of differing pharmacokinetic profiles [ see Warnings and Precautions (5.3)].

2.2 Recommended Dosage for Restless Legs Syndrome

The recommended dosage for HORIZANT is 600 mg once daily at about 5 PM. A daily dose of 1,200 mg provided no additional benefit compared with the 600-mg dose, but caused an increase in adverse reactions [see Adverse Reactions (6.1)] .

If the dose is not taken at the recommended time, the next dose should be taken the following day as prescribed.

2.3 Recommended Dosage for Postherpetic Neuralgia

The recommended dosage of HORIZANT is 600 mg twice daily. HORIZANT should be initiated at a dose of 600 mg in the morning for 3 days of therapy, then increased to 600 mg twice daily (1,200 mg/day) on day four. In the 12-week principal efficacy study, additional benefit of using doses greater than 1,200 mg a day was not demonstrated, and these higher doses resulted in an increase in adverse reactions [see Adverse Reactions (6.1)] .

If the dose is not taken at the recommended time, skip this dose, and the next dose should be taken at the time of the next scheduled dose.

2.4 Recommended Dosage for Renal Impairment

Dosing of HORIZANT is adjusted in accordance with renal function, as represented by creatinine clearance [see Clinical Pharmacology (12.3)] . Target dose regimens are listed in Table 1 and Table 2.

Table 1. Dosage of HORIZANT for Patients With Restless Legs Syndrome in Accordance With Creatinine Clearance
Creatinine Clearance (mL/min) | Target Dose Regimen
≥60 | 600 mg per day
30 – 59 | Start at 300 mg per day and increase to 600 mg as needed
15 – 29 | 300 mg per day
<15 | 300 mg every other day
<15 on hemodialysis | Not recommended

Table 2. Dosage of HORIZANT for Patients With Postherpetic Neuralgia in Accordance With Creatinine Clearance
Creatinine Clearance (mL/min) | Titration | Maintenance | Tapering
≥60 | 600 mg in AM for 3 days | 600 mg twice daily | 600 mg in AM for 1 week
30 – 59 | 300 mg in AM for 3 days | 300 mg twice daily. Increase to 600 mg twice daily as needed [Based on tolerability and efficacy] | Reduce current maintenance dose to once daily in AM for 1 week
15 – 29 | 300 mg in AM on Day 1 and Day 3 | 300 mg in AM. Increase to 300 mg twice daily if needed | If taking 300 mg twice daily, reduce to 300 mg once daily in AM for 1 week. If taking 300 mg once daily, no taper needed.
<15 | None | 300 mg every other day in AM. Increase to 300 mg once daily in AM if needed | None
<15 on hemodialysis | None | 300 mg following every dialysis. Increase to 600 mg following every dialysis if needed | None

In patients with stable renal function, CrCl can be estimated using the equation of Cockcroft and Gault:

for males: CrCl = (140-age)(weight)/[(72)(SCr)]

for females: CrCl = (0.85)(140-age)(weight)/[(72)(SCr)]

where age is in years, weight is in kilograms, and SCr is serum creatinine in mg/dL.

3 DOSAGE FORMS AND STRENGTHS

HORIZANT Extended-Release Tablets, 300 mg, are white to off-white, oval-shaped tablets debossed with "GS TF7" and 600 mg, are white to off-white, oval-shaped tablets debossed with "GS LFG". Both the 300 mg and 600 mg tablets may contain occasional black/grey spots.

4 CONTRAINDICATIONS

None.

5 WARNINGS AND PRECAUTIONS

5.1 Effects on Driving

HORIZANT may cause significant driving impairment [see Clinical Studies (14.3)] . The duration of driving impairment after starting therapy with HORIZANT is unknown. Patients taking HORIZANT should not drive until they have gained sufficient experience to assess whether HORIZANT impairs their ability to drive. However, prescribers and patients should be aware that patients' ability to assess their own driving competence, as well as their ability to assess the degree of somnolence caused by HORIZANT, can be imperfect. Whether the impairment is related to somnolence [see Warnings and Precautions (5.2)] or other effects of HORIZANT is unknown.

5.2 Somnolence/Sedation and Dizziness

HORIZANT causes somnolence/sedation and dizziness (see Tables 4and 5). Patients should be advised not to drive a car or operate other complex machinery until they have gained sufficient experience on HORIZANT to assess whether HORIZANT impairs their ability to perform these tasks.

During the controlled trials in patients with RLS, somnolence/sedation was reported in 20% of patients treated with 600 mg of HORIZANT per day compared with 6% of patients receiving placebo. In those patients treated with HORIZANT who reported somnolence, the somnolence persisted during treatment in about 30%. In the remaining patients, symptoms resolved within 3 to 4 weeks. Dizziness was reported in 13% of patients receiving 600 mg of HORIZANT per day compared with 4% of patients receiving placebo. In those patients treated with HORIZANT who reported dizziness, symptoms persisted during treatment in about 20%. Somnolence/sedation led to withdrawal in 2% of patients receiving 600 mg of HORIZANT per day. Dizziness led to withdrawal in 1% of patients receiving 600 mg of HORIZANT per day. The incidence of these adverse reactions was greater in the patients receiving 1,200 mg per day.

During the 12-week, controlled study in patients with PHN, somnolence was reported in 10% of patients treated with 1,200 mg of HORIZANT per day compared with 8% of patients receiving placebo. Fatigue/asthenia was reported in 6% of patients treated with 1,200 mg of HORIZANT per day compared with 1% of patients receiving placebo. In those patients treated with 1,200 mg of HORIZANT per day who reported somnolence (10%), the somnolence persisted during treatment in about 27%. In the remaining patients, symptoms resolved within 4 to 5 weeks. Dizziness was reported in 17% of patients receiving 1,200 mg of HORIZANT per day compared with 15% of patients receiving placebo. In those patients treated with 1,200 mg of HORIZANT per day who reported dizziness, symptoms persisted during treatment in about 6%. Somnolence led to withdrawal in <1% of patients receiving 1,200 mg of HORIZANT per day compared with 2% of patients receiving placebo. Dizziness led to withdrawal in 2% of patients receiving 1,200 mg of HORIZANT per day compared with 3% of patients receiving placebo.

5.3 Lack of Substitutability With Gabapentin

HORIZANT is not substitutable with other gabapentin products because of differing pharmacokinetic profiles. The same dose of HORIZANT results in different plasma concentrations of gabapentin relative to other gabapentin products [see Clinical Pharmacology (12.3)].

The safety and effectiveness of HORIZANT in patients with epilepsy have not been studied.

5.4 Suicidal Behavior and Ideation

HORIZANT (gabapentin enacarbil) is a prodrug of gabapentin, an antiepileptic drug (AED). AEDs increase the risk of suicidal thoughts or behavior in patients taking these drugs for any indication. Suicidal behavior and ideation have also been reported in patients after discontinuation of gabapentin [see Warnings and Precautions (5.5)] . Because HORIZANT is a prodrug of gabapentin, HORIZANT also increases this risk. Patients treated with any AED for any indication should be monitored for the emergence or worsening of depression, suicidal thoughts or behavior, and/or any unusual changes in mood or behavior.

Pooled analyses of 199 placebo-controlled clinical trials (monotherapy and adjunctive therapy) of 11 different AEDs showed that patients randomized to 1 of the AEDs had approximately twice the risk [adjusted relative risk 1.8, 95% confidence interval (CI): 1.2, 2.7] of suicidal thinking or behavior compared with patients randomized to placebo. In these trials, which had a median treatment duration of 12 weeks, the estimated incidence rate of suicidal behavior or ideation among 27,863 AED-treated patients was 0.43%, compared with 0.24% among 16,029 placebo-treated patients, representing an increase of approximately 1 case of suicidal thinking or behavior for every 530 patients treated. There were 4 suicides in drug-treated patients in the trials and none in placebo-treated patients, but the number is too small to allow any conclusion about drug effect on suicide.

The increased risk of suicidal thoughts or behavior with AEDs was observed as early as 1 week after starting drug treatment with AEDs and persisted for the duration of treatment assessed. Because most trials included in the analysis did not extend beyond 24 weeks, the risk of suicidal thoughts or behavior beyond 24 weeks could not be assessed.

The risk of suicidal thoughts or behavior was generally consistent among drugs in the data analyzed. The finding of increased risk with AEDs of varying mechanisms of action and across a range of indications suggests that the risk applies to all AEDs used for any indication. The risk did not vary substantially by age (5 to 100 years) in the clinical trials analyzed. Table 3 shows absolute and relative risk by indication for all evaluated AEDs.

Table 3. Risk by Indication for Antiepileptic Drugs in the Pooled Analysis
Indication | Placebo Patients With Events Per 1,000 Patients | Drug Patients With Events Per 1,000 Patients | Relative Risk: Incidence of Events in Drug Patients/Incidence in Placebo Patients | Risk Difference: Additional Drug Patients With Events Per 1,000 Patients
Epilepsy | 1.0 | 3.4 | 3.5 | 2.4
Psychiatric | 5.7 | 8.5 | 1.5 | 2.9
Other | 1.0 | 1.8 | 1.9 | 0.9
Total | 2.4 | 4.3 | 1.8 | 1.9

The relative risk for suicidal thoughts or behavior was higher in clinical trials for epilepsy than in clinical trials for psychiatric or other conditions, but the absolute risk differences were similar for the epilepsy and psychiatric indications.

Anyone considering prescribing HORIZANT must balance the risk of suicidal thoughts or behavior with the risk of untreated illness. Epilepsy and many other illnesses for which AEDs are prescribed are themselves associated with morbidity and mortality and an increased risk of suicidal thoughts and behavior. Should suicidal thoughts and behavior emerge during treatment, the prescriber needs to consider whether the emergence of these symptoms in any given patient may be related to the illness being treated.

Patients, their caregivers, and families should be informed that HORIZANT increases the risk of suicidal thoughts and behavior and should be advised of the need to be alert for the emergence or worsening of the signs and symptoms of depression, any unusual changes in mood or behavior, or the emergence of suicidal thoughts, behavior, or thoughts about self-harm.

Behaviors of concern should be reported immediately to healthcare providers.

5.5 Increased Risk of Seizures and Other Adverse Reactions with Abrupt or Rapid Discontinuation

Abrupt or rapid discontinuation of gabapentinoids may increase the risk for seizures.

When discontinuing HORIZANT, patients with RLS receiving 600 mg or less once daily can discontinue the drug without tapering. If the recommended dose is exceeded, the dose should be reduced to 600 mg daily for 1 week prior to discontinuation to minimize the potential of withdrawal seizure.

In patients with PHN receiving HORIZANT twice daily, the dose should be reduced to once daily for 1 week prior to discontinuation to minimize the potential of withdrawal seizure, see Table 2 [see Dosage and Administration (2.4)] .

After discontinuation of short-term and long-term treatment with gabapentin, withdrawal symptoms have been observed in some patients [see Adverse Reactions (6.2) and Drug Abuse and Dependence (9.3)] . Suicidal behavior and ideation have been reported after discontinuation of gabapentin [see Warnings and Precautions (5.4)] .

5.6 Respiratory Depression

There is evidence from case reports, human studies, and animal studies associating gabapentin with serious, life-threatening, or fatal respiratory depression when co-administered with central nervous system (CNS) depressants, including opioids, or in the setting of underlying respiratory impairment. When the decision is made to co-prescribe HORIZANT with another CNS depressant, particularly an opioid, or to prescribe HORIZANT to patients with underlying respiratory impairment, monitor patients for symptoms of respiratory depression and sedation, and consider initiating HORIZANT at a low dose. The management of respiratory depression may include close observation, supportive measures, and reduction or withdrawal of CNS depressants (including HORIZANT).

5.7 Drug Reaction With Eosinophilia and Systemic Symptoms (DRESS)/Multiorgan Hypersensitivity

Drug Reaction with Eosinophilia and Systemic Symptoms (DRESS), also known as multiorgan hypersensitivity, has been reported in patients taking antiepileptic drugs, including gabapentin. HORIZANT is a prodrug of gabapentin. Some of these events have been fatal or life-threatening. DRESS typically, although not exclusively, presents with fever, rash, lymphadenopathy, and/or facial swelling, in association with other organ system involvement, such as hepatitis, nephritis, hematological abnormalities, myocarditis, or myositis sometimes resembling an acute viral infection. Eosinophilia is often present. Because this disorder is variable in its expression, other organ systems not noted here may be involved.

It is important to note that early manifestations of hypersensitivity, such as fever or lymphadenopathy, may be present even though rash is not evident. If such signs or symptoms are present, the patient should be evaluated immediately. HORIZANT should be discontinued if an alternative etiology for the signs or symptoms cannot be established.

5.8 Tumorigenic Potential

In an oral carcinogenicity study, gabapentin enacarbil increased the incidence of pancreatic acinar cell adenoma and carcinoma in male and female rats [see Nonclinical Toxicology (13.1)] . The clinical significance of this finding is unknown.

In clinical studies of gabapentin as adjunctive therapy in epilepsy comprising 2,085 patient-years of exposure in patients >12 years of age, new tumors were reported in 10 patients (2 breast, 3 brain, 2 lung, 1 adrenal, 1 non-Hodgkin's lymphoma, 1 endometrial carcinoma in situ), and preexisting tumors worsened in 11 patients (9 brain, 1 breast, 1 prostate) during or up to 2 years following discontinuation of gabapentin. Without knowledge of the background incidence and recurrence in a similar population not treated with gabapentin, it is impossible to know whether the incidence reported in this cohort is or is not affected by treatment.

6 ADVERSE REACTIONS

The following clinically significant adverse reactions are described in more detail in the Warnings and Precautionssection of the labeling:

- Effects on Driving [see Warnings and Precautions (5.1)]
- Somnolence/Sedation and Dizziness [see Warnings and Precautions (5.2)]
- Suicidal Behavior and Ideation [see Warnings and Precautions (5.4)]
- Increased Risk of Seizures and Other Adverse Reactions with Abrupt or Rapid Discontinuation [see Warnings and Precautions (5.5)]
- Respiratory Depression [see Warnings and Precautions (5.6)]
- Drug Reaction With Eosinophilia and Systemic Symptoms (DRESS)/Multiorgan Hypersensitivity [see Warnings and Precautions (5.7)]

6.1 Clinical Trials Experience

Because clinical trials are conducted under widely varying conditions, adverse reaction rates observed in the clinical trials of a drug cannot be directly compared with rates in the clinical trials of another drug and may not reflect the rates observed in practice.

In all controlled and uncontrolled trials across various patient populations, more than 2,300 patients have received HORIZANT orally in daily doses ranging from 600 to 3,600 mg.

Restless Legs Syndrome

The exposure to HORIZANT in 1,201 patients with RLS included 613 exposed for at least 6 months and 371 exposed for at least 1 year. HORIZANT in the treatment of RLS was studied primarily in placebo-controlled trials (n = 642), and in long- term follow-up studies. The population with RLS ranged from 18 to 82 years of age, with 60% being female and 95% being Caucasian.

The safety of HORIZANT in doses ranging from 600 to 2,400 mg has been evaluated in 515 patients with RLS in 3 double-blind, placebo-controlled, 12-week clinical trials. The 600-mg dose was studied in 2 of the 3 studies. Eleven out of 163 (7%) patients treated with 600 mg of HORIZANT discontinued treatment due to adverse reactions compared with 10 of the 245 (4%) patients who received placebo.

The most commonly observed adverse reactions (≥5% and at least 2 times the rate of placebo) in these trials for the 600-mg dose of HORIZANT were somnolence/sedation and dizziness (see Table 4). Table 4 lists treatment-emergent adverse reactions that occurred in ≥2% of patients with RLS treated with HORIZANT and numerically greater than placebo.

Table 4. Incidence of Adverse Reactions in 12-Week RLS Studies Reported in ≥2% of Patients Treated With 600 or 1,200 mg of HORIZANT and Numerically Greater Than Placebo
Body System/Adverse Reaction | Placebo a (N = 245) % | HORIZANT 600 mg/day b (N = 163) % | HORIZANT 1,200 mg/day c (N = 269) %
Nervous system disorders
Somnolence/sedation | 6 | 20 | 27
Dizziness | 4 | 13 | 22
Headache | 11 | 12 | 15
Gastrointestinal disorders
Nausea | 5 | 6 | 7
Dry mouth | 2 | 3 | 4
Flatulence | <1 | 3 | 2
General disorders and administration site conditions
Fatigue | 4 | 6 | 7
Irritability | 1 | 4 | 4
Feeling drunk | 0 | 1 | 3
Feeling abnormal | <1 | <1 | 3
Peripheral edema | 1 | <1 | 3
Metabolism and nutritional disorders
Weight increased | 2 | 2 | 3
Increased appetite | <1 | 2 | 2
Ear and labyrinth disorders
Vertigo | 0 | 1 | 3
Psychiatric disorders
Depression | <1 | <1 | 3
Libido decreased | <1 | <1 | 2

aPlacebo was a treatment arm in each of the 3 double-blind, placebo-controlled, 12-week clinical trials.
bThe 600-mg dose of HORIZANT was a treatment arm in 2 of the 3 double-blind, placebo-
controlled, 12-week clinical trials.
cThe 1,200-mg dose of HORIZANT was a treatment arm in each of the 3 double-blind, placebo-controlled, 12-week clinical trials.

Adverse reactions reported in these three 12-week studies in <2% of patients treated with 600 mg of HORIZANT and numerically greater than placebo were balance disorder, blurred vision, disorientation, feeling drunk, lethargy, and vertigo.

The following adverse reactions were dose-related: somnolence/sedation, dizziness, feeling drunk, libido decreased, depression, headache, peripheral edema, and vertigo.

Postherpetic Neuralgia

The exposure to HORIZANT in 417 patients with PHN included 207 patients exposed for at least 3 months. Overall, the mean age of patients in the PHN studies ranged from 61 to 64 years of age across dose groups; the majority of patients were male (45% to 61%) and Caucasian (80% to 98%).

The safety of HORIZANT in doses ranging from 1,200 to 3,600 mg has been evaluated in 417 patients with PHN in 3 clinical studies. The principal efficacy study evaluating the efficacy and safety of HORIZANT in the management of PHN was a 12-week, double-blind, multicenter study comparing 1,200 mg/day, 2,400 mg/day and 3,600 mg/day to placebo. Six out of 107 (6%) patients treated with 1,200 mg of HORIZANT discontinued treatment due to adverse events compared with 12 of the 95 (13%) patients who received placebo.

The most commonly observed adverse reactions (≥10% and greater than placebo) in this trial for the 1,200 mg dose of HORIZANT were dizziness, somnolence, and headache (see Table 5). Table 5 lists treatment-emergent adverse reactions that occurred in ≥2% of patients with PHN treated with HORIZANT 1,200 mg/day and numerically greater than placebo.

Table 5. Incidence of Adverse Reactions (in At Least 2% of Patients Treated With 1,200 mg/day of HORIZANT and Numerically Greater Than the Placebo Rate) Reported in All Patients in the 12-Week PHN Study
Body System/Adverse Reaction | Placebo (N = 95) % | HORIZANT 1,200 mg/day (N = 107) % | HORIZANT 2,400 mg/day (N = 82) % | HORIZANT 3,600 mg/day (N = 87) %
Nervous System
Dizziness | 15 | 17 | 26 | 30
Somnolence | 8 | 10 | 11 | 14
Headache | 9 | 10 | 10 | 7
Gastrointestinal disorders
Nausea | 5 | 8 | 4 | 9
General disorders and administration site conditions
Fatigue/Asthenia | 1 | 6 | 4 | 10
Peripheral edema | 0 | 6 | 7 | 6
Psychiatric disorders
Insomnia | 2 | 3 | 5 | 7
Metabolism and nutritional disorders
Weight increased | 1 | 3 | 5 | 5
Eye disorders
Blurred vision | 0 | 2 | 5 | 2

The following adverse reactions were also reported as ≥2% at 2,400 mg/day and/or 3,600 mg/day and appeared to be dose-related but were <2% at 1,200 mg/day: balance disorder, confusional state, depression, dry mouth, flatulence, increased appetite, irritability, and vertigo. Dizziness, somnolence, fatigue, and insomnia appeared to show a dose relationship.

6.2 Postmarketing Experience

The following adverse reactions have been reported in patients receiving gabapentin and have been identified during postapproval use of HORIZANT. Because these reactions are reported voluntarily from a population of uncertain size, it is not always possible to reliably estimate their frequency or establish a causal relationship to drug exposure: breast enlargement, gynecomastia, elevated creatine kinase, bullous pemphigoid.

There are postmarketing reports of life-threatening or fatal respiratory depression in patients taking gabapentin with opioids or other CNS depressants, or in the setting of underlying respiratory impairment [see Warnings and Precautions (5.6)].

There are postmarketing reports of withdrawal symptoms after discontinuation of gabapentin. Reported adverse reactions include, but are not limited to, seizures, depression, suicidal ideation and behavior, agitation, confusion, disorientation, psychotic symptoms, anxiety, insomnia, nausea, pain, sweating, tremor, headache, dizziness, and malaise [see Warnings and Precautions (5.5)].

7 DRUG INTERACTIONS

Gabapentin enacarbil is released faster from HORIZANT Extended-Release tablets in the presence of alcohol. Consumption of alcohol is not recommended when taking HORIZANT [see Clinical Pharmacology (12.3)] .

Morphine: HORIZANT taken in conjunction with morphine causes increased somnolence/sedation, dizziness, and nausea when compared with either drug alone [see Clinical Pharmacology (12.3)].

8 USE IN SPECIFIC POPULATIONS

8.1 Pregnancy

Risk Summary

There are no adequate data on the developmental risk associated with the use of HORIZANT in pregnant women. In nonclinical studies in rats and rabbits, administration of gabapentin enacarbil was developmentally toxic when administered to pregnant animals at doses and gabapentin exposures greater than those used clinically [see Data] .

Postmarketing data suggest that extended gabapentin use with opioids close to delivery may increase the risk of neonatal withdrawal versus opioids alone. Although there is at least one report of neonatal withdrawal syndrome in an infant exposed to gabapentin alone during pregnancy, there are no comparative epidemiologic studies evaluating this association. Therefore, whether exposure to gabapentin alone late in pregnancy may cause withdrawal signs and symptoms is not known [see Clinical Considerations].

In the US general population, the estimated background risk of major birth defects and miscarriage in clinically recognized pregnancies is 2 to 4% and 15 to 20%, respectively. The background risk of major birth defects and miscarriage for the indicated population is unknown.

Clinical Considerations

Fetal/Neonatal Adverse Reactions

Neonatal withdrawal syndrome has been reported in newborns exposed to gabapentin in utero for an extended period of time when also exposed to opioids close to delivery. Neonatal withdrawal signs and symptoms reported have included tachypnea, vomiting, diarrhea, hypertonia, irritability, sneezing, poor feeding, hyperactivity, abnormal sleep pattern, and tremor. Reported signs and symptoms that may also be related to withdrawal include tongue thrusting, wandering eye movements while awake, back arching, and continuous extremity movements. Observe neonates exposed to HORIZANT and opioids for signs and symptoms of neonatal withdrawal and manage accordingly.

Data

Animal data

When pregnant rats were administered gabapentin enacarbil (oral doses of 200, 1,000, or 5,000 mg/kg/day) throughout the period of organogenesis, embryofetal mortality was increased at the 2 highest doses and fetal body weights were decreased at the high dose. The no-effect dose for embryofetal developmental toxicity in rats (200 mg/kg/day) represents approximately 2 times the gabapentin exposure associated with the maximum recommended human dose (MRHD) of 1,200 mg/day gabapentin enacarbil on an area under the curve (AUC) basis.

When pregnant rabbits were administered gabapentin enacarbil (oral doses of 200, 500, or 2,500 mg/kg/day) throughout the period of organogenesis, embryofetal mortality was increased and fetal body weights were decreased at the high dose. The no-effect dose for embryofetal developmental toxicity in rabbits (500 mg/kg/day) represents approximately 9 times the gabapentin exposure associated with the MRHD of 1,200 mg/day gabapentin enacarbil on an AUC basis.

When female rats were administered gabapentin enacarbil (oral doses of 200, 1,000, or 5,000 mg/kg/day) throughout the pregnancy and lactation periods, offspring growth and survival were decreased at the two highest doses. The no-effect dose for pre- and post-natal developmental toxicity in rats is approximately 2 times the MRHD on an AUC basis.

In reproductive and developmental studies of gabapentin, developmental toxicity was observed at all doses tested. Increased incidences of hydroureter and/or hydronephrosis were observed in rat offspring following treatment of pregnant animals in studies of fertility and general reproductive performance, embryofetal development, and peri- and post-natal development. Overall, a no-effect dose was not established. In mice, treatment of pregnant animals with gabapentin during the period of organogenesis resulted in delayed fetal skeletal ossification at all but the lowest dose tested. When pregnant rabbits were treated with gabapentin during the period of organogenesis, an increase in embryofetal mortality was observed at all doses of gabapentin tested.

In a published study, gabapentin (400 mg/kg/day) was administered by intraperitoneal injection to neonatal mice during the first postnatal week, a period of synaptogenesis in rodents (corresponding to the last trimester of pregnancy in humans). Gabapentin caused a marked decrease in neuronal synapse formation in brains of intact mice and abnormal neuronal synapse formation in a mouse model of synaptic repair. Gabapentin has been shown in vitroto interfere with activity of the α2δ subunit of voltage-activated calcium channels, a receptor involved in neuronal synaptogenesis. The clinical significance of these findings is unknown.

8.2 Lactation

Risk Summary

It is not known whether gabapentin derived from HORIZANT is secreted in human milk; however, gabapentin is secreted into human milk following oral administration of other gabapentin products. There are no data on the effects of gabapentin on the breastfed infant or the effects on milk production. The developmental and health benefits of breastfeeding should be considered along with the mother's clinical need for HORIZANT and any potential adverse effects on the breastfed infant from HORIZANT or from the underlying maternal condition.

8.4 Pediatric Use

Safety and effectiveness in pediatric patients have not been studied.

8.5 Geriatric Use

Of the 515 patients treated with HORIZANT in the 3 double-blind, placebo-controlled, 12-week clinical trials for RLS, 11% were 65 to 74 years of age and 1% were 75 years of age and older. Clinical trials of HORIZANT for the treatment of RLS did not include a sufficient number of patients 65 years and older to determine whether they respond differently from younger individuals.

In the 12-week, double-blind, placebo-controlled study of HORIZANT for the management of PHN (n = 276 patients treated with HORIZANT), 37% were 65 to 74 years of age and 13% were 75 years of age and older. The overall incidence of adverse events was comparable between the patients aged ≥18 to <65 years and ≥65 to <74 years. No overall differences in the safety and effectiveness were observed between these subjects and younger subjects, and other reported clinical experience has not identified differences in responses between the elderly and younger patients, but greater sensitivity of some older individuals cannot be ruled out.

Gabapentin is known to be almost exclusively excreted by the kidney, and the risk of adverse reactions to this drug may be greater in patients with impaired renal function. Because elderly patients are more likely to have decreased renal function, the frequency of dosing may need to be adjusted based on calculated creatinine clearance in these patients [see Dosage and Administration (2.4)] .

8.6 Renal Impairment

The dose of HORIZANT should be adjusted in patients with renal impairment [see Dosage and Administration (2.4), Clinical Pharmacology (12.3)] .

9 DRUG ABUSE AND DEPENDENCE

9.1 Controlled Substance

HORIZANT contains gabapentin enacarbil, a prodrug of gabapentin, which is not a controlled substance.

9.2 Abuse

Abuse is the intentional, non-therapeutic use of a drug, even once, for its desirable psychological or physiological effects. Misuse is the intentional use, for therapeutic purposes, of a drug by an individual in a way other than prescribed by a health care provider or for whom it was not prescribed. Gabapentin does not exhibit affinity for benzodiazepine, opioid (mu, delta, or kappa), or cannabinoid 1 receptor sites. A small number of postmarketing cases report gabapentin misuse and abuse. These individuals were taking higher than recommended doses of gabapentin for unapproved uses. Most of the individuals described in these reports had a history of poly- substance abuse or used gabapentin to relieve symptoms of withdrawal from other substances.

When prescribing products that deliver gabapentin, carefully evaluate patients for a history of drug abuse and observe them for signs and symptoms of gabapentin misuse or abuse (e.g., development of tolerance, self-dose escalation, and drug-seeking behavior).

9.3 Dependence

Physical dependence is a state that develops as a result of physiological adaptation in response to repeated drug use, manifested by withdrawal signs and symptoms after abrupt discontinuation or a significant dose reduction of a drug. After discontinuation of short-term and long-term treatment with gabapentin, withdrawal symptoms have been observed in some patients. Withdrawal symptoms may occur shortly after discontinuation, usually within 48 hours. In the postmarketing setting, reported adverse reactions have included, but not been limited to, seizures, depression, suicidal ideation and behavior, agitation, confusion, disorientation, psychotic symptoms, anxiety, insomnia, nausea, pain, sweating, tremor, headache, dizziness, and malaise. The dependence and abuse potential of gabapentin has not been evaluated in human studies.

10 OVERDOSAGE

10.1 Human Overdose Experience

The incidence of central nervous system adverse reactions, particularly dizziness and somnolence/sedation, is increased with HORIZANT doses greater than 600 mg daily.

Acute oral overdoses of gabapentin have been reported. Symptoms have included double vision, tremor, slurred speech, drowsiness, altered mental status, dizziness, lethargy, and diarrhea. Fatal respiratory depression has been reported with gabapentin overdose, alone and in combination with other CNS depressants.

10.2 Overdosage Management

In the event of an overdose, the patient should be treated supportively with appropriate monitoring as necessary. Gabapentin derived from gabapentin enacarbil can be removed from plasma by hemodialysis. The mean percentage of gabapentin recovered following hemodialysis in patients with end-stage renal disease was 29% (expressed as a proportion of the gabapentin released from HORIZANT).

Further management should be as clinically indicated or as recommended by a poison control center.

11 DESCRIPTION

HORIZANT (gabapentin enacarbil) is a prodrug of gabapentin. Gabapentin enacarbil is described as (1-{[({(1 RS)-1-[(2-Methylpropanoyl)oxy]ethoxy}carbonyl)amino]methyl} cyclohexyl) acetic acid. It has a molecular formula of C16H27NO6and a molecular weight of 329.39. It is a racemate and has the following structural formula:

Gabapentin enacarbil is a white to off-white crystalline solid with a melting onset of approximately 64°C and a solubility of 0.5 mg/mL in water and 10.2 mg/mL in phosphate buffer (pH 6.3).

HORIZANT is administered orally. Each HORIZANT Extended-Release Tablet contains 300 mg or 600 mg of gabapentin enacarbil and the following inactive ingredients: colloidal silicon dioxide, dibasic calcium phosphate dihydrate, glyceryl behenate, magnesium stearate, sodium lauryl sulfate, and talc.

12 CLINICAL PHARMACOLOGY

12.1 Mechanism of Action

Gabapentin enacarbil is a prodrug of gabapentin and, accordingly, its therapeutic effects in RLS and PHN are attributable to gabapentin.

The precise mechanism by which gabapentin is efficacious in RLS and PHN is unknown.

The mechanism of action by which gabapentin is efficacious in PHN is unknown but in animal models of analgesia, gabapentin prevents allodynia (pain-related behavior in response to a normally innocuous stimulus) and hyperalgesia (exaggerated response to painful stimuli). Gabapentin prevents pain-related responses in several models of neuropathic pain in rats and mice (e.g., spinal nerve ligation models, spinal cord injury model, acute herpes zoster infection model). Gabapentin also decreases pain-related responses after peripheral inflammation (carrageenan footpad test, late phase of formalin test), but does not alter immediate pain-related behaviors (rat tail flick test, formalin footpad acute phase). The relevance of these models to human pain is not known.

Gabapentin is structurally related to the neurotransmitter gamma-aminobutyric acid (GABA) but has no effect on GABA binding, uptake, or degradation. Gabapentin enacarbil and gabapentin have been tested in radioligand binding assays, and neither exhibited affinity for a number of other common receptor, ion channel, or transporter proteins.

In vitrostudies have shown that gabapentin binds with high affinity to the α2δ subunit of voltage-activated calcium channels; however, the relationship of this binding to the therapeutic effects of gabapentin enacarbil in RLS and PHN is unknown.

12.2 Pharmacodynamics

Cardiac Electrophysiology

At a dose of 6,000 mg, gabapentin enacarbil does not prolong QTc to a clinically relevant extent.

12.3 Pharmacokinetics

HORIZANT is an extended-release formulation of gabapentin enacarbil, a prodrug of gabapentin. HORIZANT provides approximately dose-proportional and extended exposure to gabapentin over the range 300 to 6,000 mg. HORIZANT and gabapentin are not substitutable because the same daily dose of each results in different plasma concentrations of gabapentin.

For subjects with PHN taking HORIZANT 600 mg twice daily, the estimated steady state mean Cmaxwas 5.35 µg/mL, mean AUC24was approximately 109 µg*hr/mL, mean Cminwas 3.63 µg/mL, and mean peak trough ratio was 1.5.

Absorption

The pathway for absorption of gabapentin enacarbil is believed to include active transport via a proton-linked monocarboxylate transporter, MCT-1. This transporter is expressed at high levels in the intestinal tract and is not saturated by administration of high doses of HORIZANT. Mean bioavailability of gabapentin (based on urinary recovery of gabapentin) for HORIZANT in the fed state is about 75%. Bioavailability under fasting conditions has been estimated by gabapentin urinary recovery to be 42% to 65%. In a food effect study, the exposure of gabapentin increased by 24%, 34%, and 44% with low, moderate, and high fat meals, respectively. The Tmaxof gabapentin after administration of 600 mg of HORIZANT was 5.0 hours in fasted subjects and 7.3 hours in fed subjects. Steady state is reached in 2 days with daily administration.

Distribution

Plasma protein binding of gabapentin has been reported to be <3%. The apparent volume of distribution of gabapentin in subjects receiving HORIZANT is 76 L.

Metabolism

After oral administration, gabapentin enacarbil undergoes extensive first-pass hydrolysis by non-specific carboxylesterases primarily in enterocytes and to a lesser extent in the liver, to form gabapentin, carbon dioxide, acetaldehyde, and isobutyric acid. Levels of gabapentin enacarbil in blood are low and transient (≤2% of corresponding gabapentin plasma levels). Released gabapentin is not appreciably metabolized in humans. Neither gabapentin enacarbil nor gabapentin are substrates, inhibitors, or inducers of the major cytochrome P450 enzymes (CYP1A2, CYP2A6, CYP2B6, CYP2C8, CYP2C9, CYP2C19, CYP2D6, CYP2E1, and CYP3A4). Gabapentin enacarbil is neither a substrate nor an inhibitor of P-glycoprotein in vitro.

Elimination

Following hydrolysis of gabapentin enacarbil, the released gabapentin is excreted unchanged by the kidney. Gabapentin renal excretion is believed to involve a component of active secretion via an organic cation transporter (OCT2) present in the kidney. In a human pharmacokinetic study with immediate release^14C gabapentin enacarbil, mean recovery of total radioactivity in urine was 94%, with 5% of the radioactive dose recovered in feces.

Apparent oral clearance (CL/F) of gabapentin from plasma after dosing of HORIZANT with food ranged from 6.0 to 9.3 L/hr. Following oral dosing of HORIZANT, plasma clearance of gabapentin is approximately proportional to creatinine clearance. Renal clearance (CLr) of gabapentin ranged from 5 to 7 L/hr, regardless of food intake or food type. The elimination half-life (t½) of gabapentin ranges from 5.1 to 6.0 hours and is unaltered by dose or following multiple doses of HORIZANT.

Specific Populations

Race:In the population pharmacokinetic study, the majority (94%) of subjects in the clinical studies was Caucasian, and no single other race was greater than 4%; therefore, the effect of race could not be studied.

Gender:There are no clinically meaningful differences in pharmacokinetics of HORIZANT between male and female patients.

Geriatric Patients:There are no clinically significant differences in pharmacokinetics of HORIZANT between geriatric patients (≥65 years of age) and younger patients (18 to <65 years of age). However, the pharmacokinetics in geriatric patients may be affected by an age-related decline in renal function [see Use in Specific Populations (8.5)] .

Renal Impairment:Gabapentin clearance after dosing with HORIZANT is approximately proportional to CrCl. Apparent oral clearance (CL/F) decreased in moderate (4.2 L/hr) and severe renal impairment patients (1.7 L/hr) compared with 6.0 to 9.3 L/hr in patients without renal impairment. Similarly, CLr was decreased to 3 and 1 L/hr in moderate and severe renal impairment patients, respectively, compared with 5 to 7 L/hr in non-renal impairment patients. Dosage reduction in patients with renal dysfunction not on dialysis is necessary.

Gabapentin is effectively removed from plasma by hemodialysis. The mean percentage of gabapentin recovered following hemodialysis in patients with end-stage renal disease was 29% (expressed as a proportion of the gabapentin released from HORIZANT). For patients with PHN on hemodialysis, dosage reduction is required [see Dosage and Administration (2.4)] . For patients with RLS on hemodialysis, treatment with HORIZANT is not recommended [see Dosage and Administration (2.4)] .

Drug Interactions

Neither gabapentin enacarbil nor gabapentin are substrates, inhibitors, or inducers of the major cytochrome P450 enzymes. Gabapentin enacarbil is neither a substrate nor an inhibitor of P-glycoprotein in vitro.

Pharmacokinetic drug-drug interaction studies were conducted to examine the potential for an interaction of gabapentin enacarbil with cimetidine and naproxen. No significant pharmacokinetic interactions were observed. No clinically relevant pharmacokinetic interactions are expected between HORIZANT and other substrates of organic cation transporter type 2 (OCT2) and monocarboxylate transporter type 1 (MCT-1).

Ethanol:An in vitrodissolution study was conducted to evaluate the impact of ethanol (5, 10, 20, and 40%), on the extended-release characteristics of HORIZANT. The in vitrostudy showed that about 63% of the total gabapentin enacarbil dose was released at 1 hour at the highest alcohol level (40%), and about 43% of total drug was released at 1 hour with 5% alcohol. Ethanol causes a more rapid release of gabapentin enacarbil from the extended-release tablets that may increase the risk for adverse events associated with HORIZANT. Consumption of alcohol is not recommended when taking HORIZANT.

Cimetidine:Gabapentin released from HORIZANT is eliminated by renal clearance via OCT2. Cimetidine is a known substrate for this same elimination pathway. Coadministration of 1,200 mg of HORIZANT once daily with cimetidine 400 mg 4 times daily showed no effect on cimetidine exposure. There was an increase in AUC of gabapentin (24%) and a decrease in renal clearance of gabapentin (20%); these effects are not expected to be clinically relevant. No clinically relevant pharmacokinetic interactions are expected between HORIZANT and other substrates of OCT2.

Naproxen:The pathway for absorption of gabapentin enacarbil includes active transport via a proton-linked MCT-1. Coadministration of 1,200 mg of HORIZANT once daily with naproxen 500 mg twice daily, a known substrate of MCT-1, showed no effect on naproxen exposure or steady-state gabapentin Cmaxand AUC. No clinically relevant pharmacokinetic interactions are expected between HORIZANT and other substrates of MCT-1.

Morphine:Administration of a single 600-mg dose of HORIZANT 2 hours after a single 60-mg dose of extended-release morphine sulfate in 18 subjects was associated with increased somnolence/sedation, dizziness, and nausea for the combination compared to HORIZANT or morphine alone as measured by the visual analog scale. No changes in Cmaxand AUC of gabapentin, morphine or its active metabolite morphine-6-glucuronide were observed.

13 NONCLINICAL TOXICOLOGY

13.1 Carcinogenesis, Mutagenesis, Impairment of Fertility

Carcinogenesis

Oral (gavage) carcinogenicity studies were conducted in mice and rats.

In mice, gabapentin enacarbil was tested at doses of 500, 2,000, or 5,000 mg/kg/day for up to 104 weeks. There was no evidence of drug-related carcinogenicity. The highest dose tested is 16 times the MRHD of 1,200 mg/day, on a plasma AUC basis.

In rats, gabapentin enacarbil was tested at doses of 500, 2,000, or 5,000 mg/kg/day for up to 97 weeks in mid-dose males, 90 weeks in high-dose males, and 104 weeks in females. The plasma exposures (AUC) for gabapentin at these doses are approximately 4, 17, and 37 times, respectively, that in humans at the MRHD. Increases in the incidence of pancreatic acinar adenoma and carcinoma were found in mid-dose males and high-dose males and females.

In 2-year dietary carcinogenicity studies of gabapentin, no evidence of drug-related carcinogenicity was observed in mice treated at doses up to 2,000 mg/kg/day. In rats, increases in the incidence of pancreatic acinar cell adenoma and carcinoma were found in male rats receiving the highest dose (2,000 mg/kg), but not at doses of 250 or 1,000 mg/kg/day. At 1,000 mg/kg/day, the plasma AUC for gabapentin is estimated to be approximately 13 times that in humans at the MRHD.

Studies designed to investigate the mechanism of gabapentin-induced pancreatic carcinogenesis in rats indicate that gabapentin stimulates DNA synthesis in rat pancreatic acinar cells in vitroand thus may be acting as a tumor promoter by enhancing mitogenic activity. It is not known whether gabapentin has the ability to increase cell proliferation in other cell types or in other species, including human.

Mutagenesis

Gabapentin enacarbil was negative in in vitrobacterial reverse mutation (Ames) and in vivorat micronucleus assays. In an in vitrohuman lymphocyte assay, there was an increase in the number of chromosomal aberrations with gabapentin enacarbil. This in vitroresponse was attributed to acetaldehyde released by hydrolysis of gabapentin enacarbil during the incubation period. Acetaldehyde is known to cause chromosome aberrations in vitro, but is readily metabolized in vivo. The small quantity of acetaldehyde formed from gabapentin enacarbil in vivois rapidly cleared by normal metabolic activity.

Impairment of Fertility

Oral administration of gabapentin enacarbil (doses of 0, 200, 1,000, or 5,000 mg/kg/day) to male and female rats prior to and throughout mating and continuing in females up to day 7 of gestation resulted in no adverse effects on fertility. The highest dose tested is approximately 39 times the MRHD on an AUC basis.

14 CLINICAL STUDIES

14.1 Restless Legs Syndrome (RLS) 12-Week Pivotal Studies

The effectiveness of HORIZANT in the treatment of moderate-to-severe primary RLS was demonstrated in two 12-week clinical studies in adults diagnosed with RLS using the International Restless Legs Syndrome Study Group diagnostic criteria. Key diagnostic criteria for RLS are: an urge to move the legs usually accompanied or caused by uncomfortable and unpleasant leg sensations, symptoms begin or worsen during periods of rest or inactivity such as lying or sitting, symptoms are partially or totally relieved by movement such as walking or stretching at least as long as the activity continues, and symptoms are worse or occur only in the evening or night. Patients were required to have a total score of ≥15 on the International Restless Legs Syndrome (IRLS) Rating Scale at baseline. Patients with RLS secondary to other conditions (e.g., pregnancy, renal failure, iron deficiency anemia) were excluded. In study 1, patients were randomized to receive 1,200 mg of HORIZANT (N = 112) or placebo (N = 108) taken once daily at about 5 PM with food. In study 2, patients were randomized to receive 600 mg of HORIZANT (N = 114), 1,200 mg of HORIZANT (N = 111), or placebo (N = 96) taken once daily at about 5 PM with food.

Efficacy was evaluated using the IRLS Rating Scale and Clinical Global Impression of Improvement (CGI-I) scores. The IRLS Rating Scale contains 10 items designed to assess the severity of sensory and motor symptoms, sleep disturbance, daytime somnolence/sedation, and impact on activities of daily living and mood associated with RLS. The range of scores is 0 to 40, with 0 being absence of RLS symptoms and 40 the most severe symptoms. The CGI-I Scale allows the investigator to rate the patient's overall change in RLS symptoms since baseline, whether or not in the opinion of the investigator the change is related to study drug treatment. The change from baseline in the IRLS Rating Scale at Week 12 and the proportion of responders on the CGI-I Scale defined as a rating of "much improved" or "very much improved" at Week 12 were co-primary outcomes in these studies.

In these 2 studies, the mean age of patients studied was 50 years (range: 18 to 81 years); 59% of the patients were female. The racial distribution for these studies was as follows: Caucasian, 95%; black, 2%; and other, 3%.

Statistically significant differences (P<0.05) between the treatment groups receiving 600 and 1,200 mg of HORIZANT and the group receiving placebo were observed at Week 12 for both the mean change from baseline in the IRLS Scale total score and the proportion of responders ("much improved" or "very much improved") on the CGI-I Scale as described in Table 6.

Table 6. Mean Change in IRLS Scale Total Score and Proportion of Responders on CGI-I Scale at Week 12
Week 12 | Study 1 |  | Study 2
Week 12 | HORIZANT 1,200 mg (N = 112) | Placebo (N = 108) | HORIZANT 600 mg (N = 114) | HORIZANT 1,200 mg (N = 111) | Placebo (N = 96)
Mean Change in IRLS Score | -13.2 | -8.8 | -13.8 | -13.0 | -9.8
Proportion of Respondersa on CGI-I | 76% | 39% | 73% | 77% | 45%

aCGI-I Responders = “much improved” and “very much improved.”

Figure 1 presents the improvement in mean IRLS Rating Scale total score in patients treated with placebo or 600 or 1,200 mg of HORIZANT over the 12 weeks of treatment in study 2.

Figure 1. Study 2, Mean (±SD) IRLS Rating Scale Total Score Over 12 Weeks (Observed Case Data, Modified Intent-To-Treat Population)

14.2 Postherpetic Neuralgia (PHN) 12-Week Study

The efficacy of HORIZANT for the management of postherpetic neuralgia was established in a multicenter, randomized, double-blind, parallel-group, placebo-controlled, 12- week study evaluating the efficacy, safety, and dose response of 3 maintenance doses of HORIZANT (1,200, 2,400, and 3,600 mg/day, with 107, 82, and 87 patients in each dosing group, respectively). Patients greater than 18 years of age with a documented medical diagnosis of PHN of at least three months duration were enrolled. To ensure that patients had significant pain, randomized patients were required to have a minimum baseline 24-hour average Pain Intensity Numerical Rating Scale (PI-NRS) intensity score of at least 4.0 on the 11-point numerical PI-NRS, ranging from 0 ("no pain") to 10 ("pain as bad as you can imagine"). In this study, a total of 276 patients received HORIZANT while 95 patients received placebo. Following a 1-week baseline period during which patients were screened for eligibility, patients began a 1-week up-titration period followed by a 12-week maintenance treatment period, and then a 1-week down-titration period. Treatment with HORIZANT statistically significantly improved the mean pain score and increased the proportion of patients with at least a 50% reduction in pain score from baseline at all doses tested. A benefit over placebo was observed for all 3 doses of HORIZANT as early as Week 1 and maintained to the end of treatment. Additional benefit of using doses of greater than 1,200 mg a day was not demonstrated. For various degrees of improvement in pain from baseline to end of maintenance treatment, Figure 2 shows the fraction of patients achieving that degree of improvement. The figure is cumulative, so that patients whose change from baseline is, for example, 50%, are also included at every level of improvement below 50%. Patients who did not complete the study were assigned 0% improvement.

Figure 2. Percent of Patients Achieving Various Levels of Improvement in Pain Intensity

14.3 Effects on Driving

Driving performance was assessed in a three way crossover study in healthy volunteers (mean age 36 years). Subjects were dosed at approximately 5 pm with HORIZANT 600 mg (for five days), diphenhydramine 50 mg (1 dose), and placebo (for five days). After the last dose, driving was evaluated on a computer-based simulation for 1 hour in the evening approximately 2 to 4 hours after dosing (7 to 9 pm), in the morning after dosing (7 to 9 am), and at midday the day after dosing (11 am to 1 pm). The primary endpoint of the study was lane position variability. There was no difference in change from baseline in lane position variability for HORIZANT compared to placebo at any of the simulated driving timepoints. Secondary measures included speed variability and the occurrence of simulated crashes. Subjects in this study experienced simulated crashes as described in Table 7. At the times that simulated crashes occurred, there was an increase in average speed variability in the HORIZANT- and diphenhydramine-treated groups that was most notable in patients who experienced simulated crashes, but no increases in lane position variability. Later time points post-dosing or the effects of driving after more than five days of dosing with HORIZANT were not evaluated.

Table 7. Simulated Crashes at Evaluated Timepoints (Secondary Measure)
Simulated Driving Timepoint and Hours Post Dose | Baseline N = 36 n (%) | Placebo N = 36 n (%) | HORIZANT 600 mg N = 35 n (%) | Diphenhydramine 50 mg N = 36 n (%)
Day 5 Evening (7 to 9 pm) 2 to 4 hours post dose | 0 (0) | 0 (0) | 0 (0) | 3 (9)
Day 6 Morning (7 to 9 am) 14 to 16 hours post dose | 2 (6) | 1 (3) | 1 (3) | 0 (0)
Day 6 Midday (11 am to 1 pm) 18 to 20 hours post dose | 1 (3) | 0 (0) | 3 (9) | 3 (8)

The results of a separate 2-week driving simulation study in patients (mean age 47 years) with moderate-to-severe primary RLS showed that once daily doses of 1,200 mg and 1,800 mg of HORIZANT significantly impaired simulated driving performance based on lane position variability. An increased number of simulated crashes were reported in patients tested near Tmaxafter receiving 1,200 mg or 1,800 mg of HORIZANT compared to patients treated with diphenhydramine 50 mg. In addition, patients receiving 1,200 mg of HORIZANT experienced an increased number of simulated crashes at 14 to 16 hours after dosing compared with placebo, diphenhydramine, and 1,800 mg of HORIZANT.

The design limitations of these two studies do not permit inference regarding dose response relationship or the duration of the effect HORIZANT has on driving in patients with RLS.

The results of a separate driving simulation study comparing untreated RLS patients and healthy subjects showed no difference in lane position variability but an increase in speed variability associated with a greater number of simulated crashes in RLS patients relative to healthy subjects, which may indicate impaired driving in RLS patients in the absence of medication.

16 HOW SUPPLIED/STORAGE AND HANDLING

HORIZANT Extended-Release Tablets containing 300 mg of gabapentin enacarbil are white to off-white, with occasional black/grey spots, oval-shaped tablets debossed with "GS TF7".

HORIZANT Extended-Release Tablets containing 600 mg of gabapentin enacarbil are white to off-white, with occasional black/grey spots, oval-shaped tablets debossed with "GS LFG". They are supplied as follows:

300 mg: NDC 53451-0103-1: Bottles of 30
600 mg: NDC 53451-0101-1: Bottles of 30

STORAGE AND HANDLING

Store at 25°C (77°F); excursions permitted 15°C to 30°C (59°F to 86°F) [see USP Controlled Room Temperature]. Protect from moisture. Do not remove desiccants.

17 PATIENT COUNSELING INFORMATION

Advise the patient to read the FDA-approved patient labeling (Medication Guide).

Effects on Driving

Patients should be told that HORIZANT may cause a significant driving impairment. Accordingly, they should be advised not to drive a car until they have gained sufficient experience on HORIZANT to assess whether HORIZANT impairs their ability to drive, although patients' ability to determine their level of impairment can be unreliable. Patients should be told that it is not known how long this effect lasts [see Warnings and Precautions (5.1)].

Somnolence/Sedation and Dizziness

Patients should be told that HORIZANT can cause significant somnolence and dizziness. This typically resolves within several weeks of initiating treatment. Accordingly, they should be told not to operate dangerous machinery until they have gained sufficient experience on HORIZANT to assess whether HORIZANT impairs their ability to operate dangerous machinery safely [see Warnings and Precautions (5.2)].

Suicidal Behavior and Ideation

Patients, their caregivers, and families should be counseled that HORIZANT may increase the risk of suicidal thoughts and behavior, and should be advised of the need to be alert for the emergence or worsening of symptoms of depression, any unusual changes in mood or behavior, or the emergence of suicidal thoughts, behavior, or thoughts about self-harm. Instruct patients to report behaviors of concern immediately to healthcare providers [see Warnings and Precautions (5.4)]. Also, inform patients who plan to or have discontinued HORIZANT that suicidal thoughts and behavior can appear even after the drug is stopped.

Respiratory Depression

Inform patients about the risk of respiratory depression. Include information that the risk is greatest for those using concomitant CNS depressants (such as opioid analgesics), or those with concurrent respiratory impairment. Teach patients how to recognize respiratory depression and advise them to seek medical attention immediately if it occurs [see Warnings and Precautions (5.5)] .

Drug Reaction With Eosinophilia and Systemic Symptoms (DRESS)/Multiorgan Hypersensitivity

Patients should be instructed that multiorgan hypersensitivity reactions may occur with HORIZANT. Patients should contact their healthcare provider immediately if they experience any signs or symptoms of these conditions [see Warnings and Precautions (5.5)] .

Lack of Substitutability With Gabapentin

Patients should be advised that doses of HORIZANT and other gabapentin products are not substitutable [see Warnings and Precautions (5.3)].

Dosing Instructions [see Dosage and Administration (2.1, 2.2, 2.3) ]

- Instruct patients to take HORIZANT only as prescribed.
- Instruct patients to swallow tablets whole and do not cut, crush, or chew tablets.
- Instruct patients to take HORIZANT with food.
- For Restless Legs Syndrome, 600 mg HORIZANT should be taken once daily at about 5 PM. If the dose is not taken at the recommended time, the patient should take the next dose at about 5 PM the following day.
- For Postherpetic Neuralgia, the starting dose is 600 mg HORIZANT in the morning for 3 days. Starting on day 4, 600 mg HORIZANT should be taken twice daily. If the dose is not taken at the recommended time, the next dose should be taken at the time of next scheduled dose.
- Instruct patients about how to discontinue HORIZANT.

Alcohol

Advise patients to avoid alcohol when taking HORIZANT [see Drug Interactions (7), Clinical Pharmacology (12.3)] .

Use in Pregnancy

Instruct patients to notify their healthcare provider if they are pregnant or intend to become pregnant during therapy and to notify their healthcare provider if they are breast feeding or intend to breast feed during therapy [ see Use in Specific Populations (8.1) and (8.2) ].

HORIZANT is a registered trademark of Azurity Pharmaceuticals, Inc.

Manufactured for:

Azurity Pharmaceuticals, Inc.
Woburn, MA 01801

Azurity Pharmaceuticals, Inc. All rights reserved.

HZT-PI-05 Rev. 04/2025

MEDICATION GUIDE

HORIZANT® (ho-ri' zant) (gabapentin
enacarbil) Extended-Release Tablets

Read this Medication Guide before you start taking HORIZANT and each time you get a refill. There may be new information. This information does not take the place of talking to your healthcare provider about your medical condition or treatment.

What is the most important information I should know about HORIZANT?

HORIZANT can cause serious side effects:

1. Do not drive after taking your dose of HORIZANT until you know how HORIZANT affects you, including the morning after you take your dose. Do notoperate heavy machinery or do other dangerous activities until you know how HORIZANT affects you. HORIZANT can cause sleepiness, dizziness, slow thinking, and can affect your coordination. Ask your healthcare provider when it would be okay to do these activities.

2. HORIZANT may cause suicidal thoughts or actions in a very small number of people, about 1 in 500. This can happen while you take HORIZANT or after stopping HORIZANT.
Call a healthcare provider right away if you have any of these symptoms, especially if they are new, worse, or worry you:

- thoughts about suicide or dying
- attempt to commit suicide
- new or worse depression
- new or worse anxiety
- feeling agitated
- new or worse restlessness
- panic attacks
- new or worse trouble sleeping (insomnia)
- new or worse irritability
- acting aggressive, being angry, or violent
- acting on dangerous impulses
- an extreme increase in activity and talking (mania)
- other unusual changes in behavior or mood

How can I watch for early symptoms of suicidal thoughts and actions?

- Pay attention to any changes, especially sudden changes, in mood, behaviors, thoughts, or feelings.
- Keep all follow-up visits with your healthcare provider as scheduled.
- Call your healthcare provider between visits as needed, especially if you are worried about symptoms.

Do not stop HORIZANT without first talking to a healthcare provider.Suicidal thoughts or actions can be caused by things other than medicines. If you have suicidal thoughts or actions, your healthcare provider may check for other causes.

3. HORIZANT may cause a serious or life-threatening allergic reaction that may affect your skin or other parts of your body such as your liver or blood cells. You may or may not have rash with these types of reactions. Call a healthcare provider right away if you have any of the following symptoms:

- skin rash
- hives
- fever
- swollen glands that do not go away
- swelling of your lips or tongue
- yellowing of your skin or eyes
- unusual bruising or bleeding
- severe fatigue or weakness
- unexpected, severe muscle pain
- frequent infections

These symptoms may be the first signs of a serious reaction. A healthcare provider should examine you to decide if you should continue taking HORIZANT.

4. Serious breathing problems. Serious breathing problems can occur when HORIZANT is taken with other medicines that can cause severe sleepiness or decreased awareness, or when it is taken by someone who already has breathing problems. Watch for increased sleepiness or decreased breathing when starting HORIZANT or when the dose is increased. Get help right away if breathing problems occur.

What is HORIZANT?

HORIZANT is a prescription medicine used to treat adults with:

- moderate-to-severe primary Restless Legs Syndrome (RLS).
- pain from damaged nerves (postherpetic pain) that follows healing of shingles (a painful rash that comes after a herpes zoster infection).

HORIZANT is not for people with RLS who need to sleep during the daytime and need to stay awake at night.

HORIZANT is not the same medicine as gabapentin (for example, NEURONTIN®or GRALISE®) and should not be used in its place.

It is not known if HORIZANT is safe and effective in children.

What should I tell my healthcare provider before taking HORIZANT?

Before taking HORIZANT, tell your healthcare provider if you:

- have or have had kidney problems or are on hemodialysis.
- have or have had depression, mood problems, or suicidal thoughts or behavior.
- have or have had seizures.
- have a history of drug abuse.
- have breathing problems.
- have any other medical conditions.
- are pregnant or plan to become pregnant.
  - It is not known if HORIZANT will harm your unborn baby. Talk to your healthcare provider if you are pregnant or plan to become pregnant while taking HORIZANT. You and your healthcare provider will decide if you should take HORIZANT while you are pregnant.
- are breastfeeding or plan to breastfeed. Your body turns HORIZANT into another drug (gabapentin) that passes into your milk. It is not known if this can harm your baby. You and your healthcare provider should decide if you will take HORIZANT or breastfeed.
- drink alcohol.

Tell your healthcare provider about all the medicines you take, including prescription and non-prescription medicines, vitamins, and herbal supplements. Especially tell your healthcare provider if you take any opioid pain medicine (such as oxycodone), any medicines for anxiety (such as lorazepam) or insomnia (such as zolpidem), or any medicines that make you sleepy.

You may have a higher chance for dizziness, sleepiness, or breathing problems if these medicines are taken with HORIZANT.

Know the medicines you take. Keep a list of them and show it to your healthcare provider and pharmacist when you get a new medicine.

How should I take HORIZANT?

- Take HORIZANT exactly as your healthcare provider tells you to take it. Your healthcare provider will tell you how much HORIZANT to take and when to take it.
- Take HORIZANT tablets whole. Do notcut, crush, or chew your tablet.
- Take HORIZANT tablets with food.
- Do not stop taking HORIZANT without talking to your healthcare provider first.If you stop taking HORIZANT suddenly, you may develop side effects.
- If you forget to take your medicine at the time recommended by your healthcare provider, just skip the missed dose. Take the next dose at your regular time. Do nottake 2 doses at one time.
- If you take too much HORIZANT, call your healthcare provider or go to the nearest hospital emergency room right away.

What should I avoid while taking HORIZANT?

- Do not take other medicines that make you sleepy or dizzy while taking HORIZANT without first talking with your healthcare provider. Taking HORIZANT with medicines that cause sleepiness or dizziness may make your sleepiness or dizziness worse.
- Do not take other gabapentin drugs (for example, NEURONTIN or GRALISE) while you take HORIZANT.
- Do not consume alcohol when taking HORIZANT.

What are the possible side effects of HORIZANT?

- See " What is the most important information I should know about HORIZANT?"

The most common side effects of HORIZANT include:

- sleepiness
- dizziness
- headache

Tell your healthcare provider if you have any side effect that bothers you or that does not go away.

These are not all the possible side effects of HORIZANT. For more information, ask your healthcare provider or pharmacist.

Call your doctor for medical advice about side effects. You may report side effects to FDA at 1-800-FDA-1088.

How should I store HORIZANT?

- Store HORIZANT between 59° and 86°F (15° and 30°C).
- Keep HORIZANT dry and away from moisture.
- Keep HORIZANT tightly closed in the bottle provided to you. Do not remove any moisture control packs that may come in the bottle.

Keep HORIZANT and all medicines out of the reach of children.

General Information about the safe and effective use of HORIZANT

Medicines are sometimes prescribed for purposes other than those listed in a Medication Guide. Do not use HORIZANT for a condition for which it was not prescribed. Do not give HORIZANT to other people, even if they have the same symptoms that you have. It may harm them.

This Medication Guide summarizes the most important information about HORIZANT. If you would like more information, talk with your healthcare provider.

You can ask your healthcare provider or pharmacist for information about HORIZANT that was written for healthcare professionals.

For more information about HORIZANT, go to www.HORIZANT.com or call 1-800-461-7449.

What are the ingredients in HORIZANT?

Active ingredients:gabapentin enacarbil

Inactive ingredients:Both the 300 mg and 600 mg tablets contain colloidal silicon dioxide, dibasic calcium phosphate dihydrate, glyceryl behenate, magnesium stearate, sodium lauryl sulfate, and talc.

Manufactured for:

Azurity Pharmaceuticals, Inc.
Woburn, MA 01801

HORIZANT is a registered trademark of Azurity Pharmaceuticals, Inc. The other brands listed are trademarks of their respective owners and are not trademarks of Azurity Pharmaceuticals, Inc. The makers of these brands are not affiliated with and do not endorse Azurity Pharmaceuticals, Inc. or its products.

HZT-MG-03 Rev. 04/2025

This Medication Guide has been approved by the U.S. Food and Drug Administration.

PRINCIPAL DISPLAY PANEL - 300 mg Tablet Bottle Label

30 Tablets
NDC 53451-0103-1

Horizant®
(gabapentin enacarbil)
extended-release tablets

300 mg

Dispense the accompanying
Medication Guide
to each patient.

Rx only

PRINCIPAL DISPLAY PANEL - 600 mg Tablet Bottle Label

30 Tablets
NDC 53451-0101-1

Horizant®
(gabapentin enacarbil)
extended-release tablets

600 mg

Dispense the accompanying
Medication Guide to each patient.

Rx only

azurity®
pharmaceuticals

HZT-TL600-02